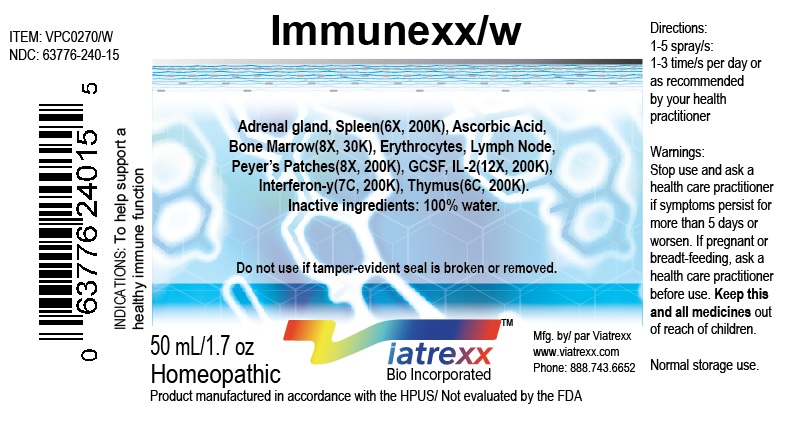 DRUG LABEL: Immunexx W
NDC: 63776-240 | Form: SPRAY
Manufacturer: VIATREXX BIO INCORPORATED
Category: homeopathic | Type: HUMAN OTC DRUG LABEL
Date: 20180111

ACTIVE INGREDIENTS: Bos Taurus Adrenal Gland 200 [kp_C]/1 mL; Sus Scrofa Adrenal Gland 200 [kp_C]/1 mL; Ascorbic Acid 30 [kp_C]/1 mL; Bos Taurus Bone Marrow 30 [kp_C]/1 mL; Sus Scrofa Bone Marrow 30 [kp_C]/1 mL; Bos Taurus Red Blood Cell 200 [kp_C]/1 mL; Sus Scrofa Red Blood Cell 200 [kp_C]/1 mL; Filgrastim 200 [kp_C]/1 mL; Aldesleukin 200 [kp_C]/1 mL; Interferon Gamma-1a 200 [kp_C]/1 mL; Bos Taurus Lymph Vessel 200 [kp_C]/1 mL; Sus Scrofa Lymph Vessel 200 [kp_C]/1 mL; Bos Taurus Peyer's Patch 200 [kp_C]/1 mL; Sus Scrofa Peyer's Patch 200 [kp_C]/1 mL; Bos Taurus Thymus 200 [kp_C]/1 mL; Sus Scrofa Thymus 200 [kp_C]/1 mL; Bos Taurus Spleen 200 [kp_C]/1 mL; Sus Scrofa Spleen 200 [kp_C]/1 mL
INACTIVE INGREDIENTS: Water

Immunexx

Active Ingredients

Adrenal gland 6X 200K, Ascorbic acid 8X 30K, Bone marrow 8X 30K, Erythrocytes 8X 200K, Granulocyte colony-stimulating factor 12X 200K, Interleukin 2 12X 200K, Interferon gamma 7C, 200K, Lymph node 8X 200K, Peyer's Patches 8X 200K, spleen 6X 200K, Thymus 6C 200K

Purpose:

Adrenal gland | Adrenal support
Ascorbic acid | Anti-oxidant
Bone marrow | Immune support
Erythrocytes | Immune support
Granulocyte colony-stimulating factor | Immune support
Interleukin 2 | Immune support
Interferon gamma | Immune support
Lymph node | Immune support
Peyer's Patches Spleen | Regeneration Regeneration
Thymus | Regeneration

Uses

To help support a healthy immune function

Warnings

Stop use and ask a health care practitioner if symptoms persist for more than five days or worsen. If pregnant or breastfeeding, ask a health care practitioner before use.

Dosage

1-3 spray(s); 1-3 time(s) per day or as recommended by your health care practitioner.

KEEP OUT OF REACH OF CHILDREN

Keep this and all medicines out of reach of children.

Other Ingredients

Alcohol and Water

Other Information

Normal storage use.
Do not use if tamper-evident seal is broken or removed.

Questions

info@viatrexx.com

Principal Display Panel

ITEM: VPC0270/w
NDC 63776-240-14
Homeopathic remedy
Immunexx W
• To help support a healthy immune function
Oral spray
30ml 1 oz
Viatrexx™ Bio Incorporated
Manufactured by Viatrexx
www.viatrexx.com
Newark, DE 19713

Immunexx W
30 mL
1 oz
Viatrexx™ Bio Incorporated
ITEM: VPC0270/w
NDC: 63776-240-14
INDICATIONS:
To help support a healthy immune function
DIRECTIONS:
1-3 spray(s); 1-3 time(s) per day or as recommended by your health care practitioner.
Mfg. for
Viatrexx Bio Incorporated.
www.viatrexx.com
Newark, DE 19713